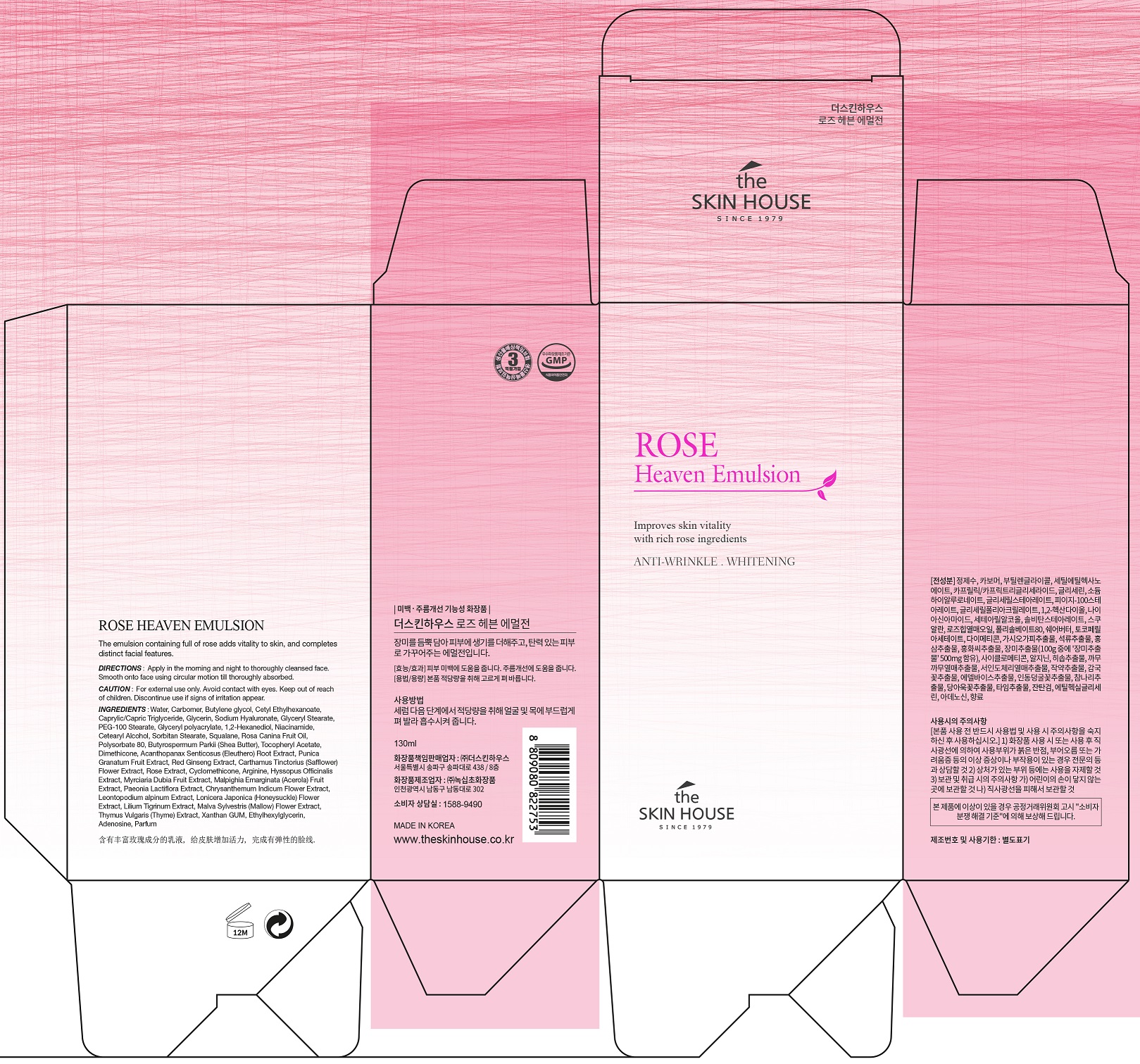 DRUG LABEL: THE SKIN HOUSE ROSE HeavenEmulsion
NDC: 73590-0049 | Form: EMULSION
Manufacturer: NOKSIBCHO cosmetic Co., Ltd.
Category: otc | Type: HUMAN OTC DRUG LABEL
Date: 20200408

ACTIVE INGREDIENTS: NIACINAMIDE 2 g/100 mL; ADENOSINE 0.04 g/100 mL
INACTIVE INGREDIENTS: WATER

Drug Facts

ACTIVE INGREDIENT

Adenosine, Niacinamide

INACTIVE INGREDIENT

Water
Carbomer
Butylene glycol
Cetyl Ethylhexanoate
Caprylic/Capric Triglyceride
Glycerin
Sodium Hyaluronate
Phenoxy ethanol
Glyceryl Stearate
PEG-100 Stearate
Glyceryl polyacrylate
1,2-Hexanediol
Cetyl Alcohol
Stearyl Alcohol
Myristyl Alcohol
Lauryl Alcohol
Sorbitan Stearate
Squalane
Rosa Canina Fruit Oil
Polysorbate 80
Butyrospermum Parkii (Shea Butter)
Tocopheryl Acetate
Dimethicone
Acanthopanax Senticosus (Eleuthero) Root Extract
Punica Granatum Fruit Extract
Carthamus Tinctorius (Safflower) Flower Extract
Propyliene glycol
Red ginseng extract
Rose Extract
Cyclomethicone
Arginine
Hyssopus Officinalis Extract
Myrciaria Dubia Fruit Extract
Malpighia Emarginata (Acerola) Fruit Extract
Paeonia Lactiflora Extract
Chrysanthemum Indicum Flower Extract
Leontopodium alpinum extract
Lonicera Japonica (Honeysuckle) Flower Extract
Lilium Tigrinum Extract
Malva Sylvestris (Mallow) Flower Extract
Thymus Vulgaris (Thyme) Extract
Xanthan GUM
Ethylhexylglycerin
Parfum

PURPOSE

anti-wrinkle, whitening

keep out of reach of the children

INDICATIONS AND USAGE

apply proper amount to the skin

WARNINGS

For external use only
When using this product

■ if the following symptoms occurs after use, stop use and consult with a skin specialist

red specks, swelling, itching

■ don’t use on the part where there is injury, eczema, or dermatitis

Keep out of reach of children

■ if swallowed, get medical help or contact a person control center immediately